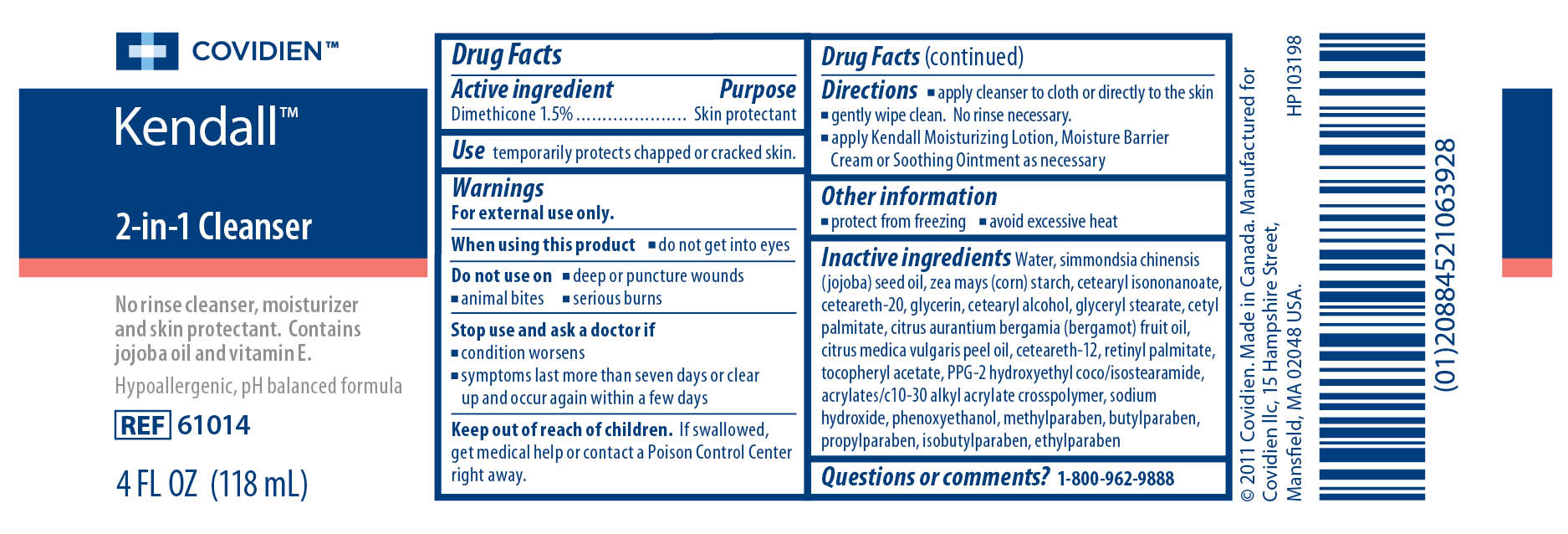 DRUG LABEL: Kendall 2-in-1 Cleanser
NDC: 28851-690 | Form: LIQUID
Manufacturer: Covidien Inc.
Category: otc | Type: HUMAN OTC DRUG LABEL
Date: 20110405

ACTIVE INGREDIENTS: Dimethicone 1.5 mL/100 mL
INACTIVE INGREDIENTS: Water; JOJOBA OIL; STARCH, CORN; CETEARYL ISONONANOATE ; POLYOXYL 20 CETOSTEARYL ETHER; GLYCERIN; CETOSTEARYL ALCOHOL; GLYCERYL MONOSTEARATE; CETYL PALMITATE ; BERGAMOT OIL ; CETEARETH-12; VITAMIN A PALMITATE; ACETATE ION; SODIUM HYDROXIDE; PHENOXYETHANOL; METHYLPARABEN; BUTYLPARABEN; PROPYLPARABEN ; ISOBUTYLPARABEN; ETHYLPARABEN

Kendall 2-in-1 Cleanser

Active Ingredient

Dimethicone 1.5%

Purpose

Skin Protectant

Use

temporarily protects chapped or cracked skin.

Warnings

For external use only.
When using this product

- do not get into eyes

Do not use on

- deep or puncture wounds
- animal bites
- serious burns

Stop use and ask a doctor if

- condition worsens
- symptoms last more than seven days or clear up and occur again within a few days

Keep out of the reach of children. If swallowed, get medical help or contact a Poison Control Center right away.

Directions

- apply cleanser to cloth or directly to the skin
- gently wipe clean. No rinse necessary.
- apply Kendall Moisturizing Lotion, Moisture Barrier Cream or Soothing Ointment as necessary

Other Information

- protect from freezing
- avoid excessive heat

Inactive ingredients

Water, simmondsia chinensis (jojoba) seed oil, zea mays (corn) starch, cetearyl isononanoate, ceteareth-20, glycerin, cetearyl alcohol, glyceryl stearate, cetyl palmitate, cirtus aurantium bergamia (bergamot) fruit oil, citrus medica vulgaris peel oil, ceteareth-12, retinyl palmitate, tocopheryl acetate, PPG-2 hydroxyethyl coco/isostearamide, acrylates/c10-30 alkyl acrylate crosspolymer, sodium hydroxide, phenoxyethanol, methylparaben, butylparaben, propylparaben, isobutylparaben, ethylparaben

Questions or comments? 1-800-962-9888

Image of 4 Ounce Label